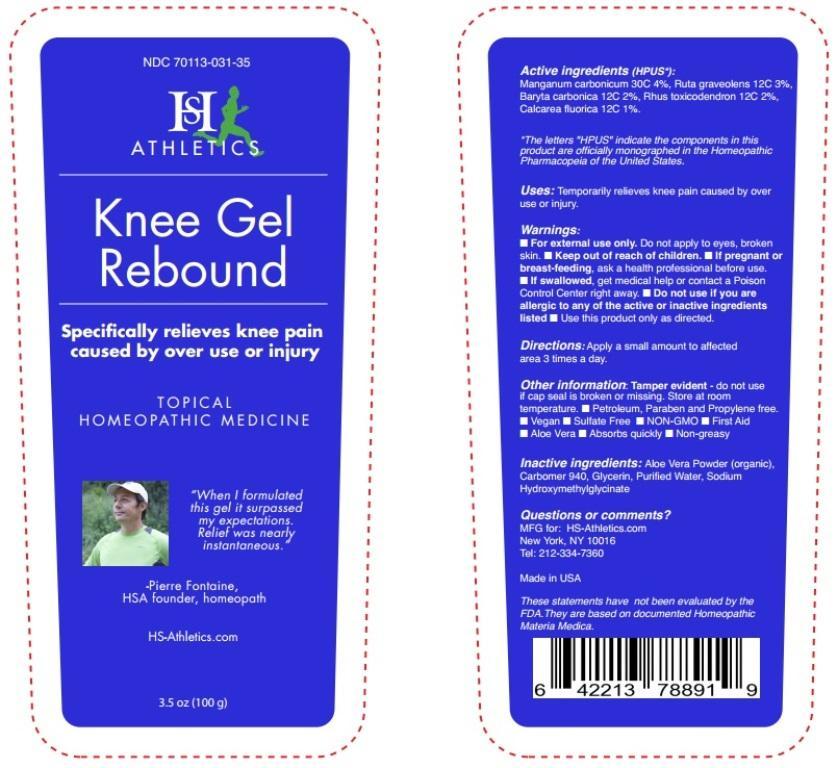 DRUG LABEL: Knee Gel Rebound
NDC: 70113-031 | Form: GEL
Manufacturer: Homeopathic Services Inc.
Category: homeopathic | Type: HUMAN OTC DRUG LABEL
Date: 20190905

ACTIVE INGREDIENTS: MANGANESE CARBONATE 30 [hp_C]/1 g; RUTA GRAVEOLENS FLOWERING TOP 12 [hp_C]/1 g; BARIUM CARBONATE 12 [hp_C]/1 g; TOXICODENDRON PUBESCENS LEAF 12 [hp_C]/1 g; CALCIUM FLUORIDE 12 [hp_C]/1 g
INACTIVE INGREDIENTS: ALOE VERA LEAF; CARBOMER HOMOPOLYMER TYPE C (ALLYL PENTAERYTHRITOL CROSSLINKED); GLYCERIN; WATER; SODIUM HYDROXYMETHYLGLYCINATE

Knee Gel Rebound

Active ingredients (HPUS*):

Manganum carbonicum 30C 4%, Ruta graveolens 12C 3%, Baryta carbonica 12C 2%, Rhus toxicodendron 12C 2%, Calcarea fluorica 12C 1%.

ACTIVE INGREDIENT

*The letters "HPUS" indicate the components in this product are officially monographed in the Homeopathic Pharmacopeia of the United States.

INDICATIONS AND USAGE

Uses: Tempoarily relieves knee pain caused by over use or injury.

These statements have not been evaluated by the FDA. They are based on documented Homeopathic Materia Medica.

Warnings:

- For external use only. Do not apply to eyes, broken skin.
- If pregnant or breast-feeding, ask a health professional before use.
- If swallowed, get medical help or contact a Poison Control Center right away.
- Do not useif you are allergic to any of the active or inactive ingredients listed.
- Use this product only as directed.

- Keep out of reach of children.

DOSAGE AND ADMINISTRATION

Directions: Apply a small amount to affected area 3 times a day.

Other information: Tamper evident - do not use if cap seal is broken or missing. Store at room temperature.

- Petroleum, Paraben and Propylene free.
- Vegan
- Sulfate Free
- NON-GMO
- First Aid
- Aloe Vera
- Absorbs quickly
- Non-greasy

INACTIVE INGREDIENT

Inactive ingredients: Aloe Vera Powder (organic), Carbomer 940. Glycerin, Purified Water, Sodium Hydroxymethylglycinate.

Questions or comments?

MFG for: HS-Athletics.com

New York, NY 10016

Tel: 212-334-7360

Made in the USA

PACKAGE LABEL

NDC 70113-031-35

HS Athletics

Knee Gel Rebound

Specifically relieves knee pain caused by over use or injury

TOPICAL HOMEOPATHIC MEDICINE

"When I formulated this gel it surpassed my expectations. Relief was nearly instantaneous."

-Pierre Fontaine,

HSA founder, homeopath

HS-Athletics.com

3.5 oz (100g)

PURPOSE

Specifically relieves knee pain caused by over use or injury